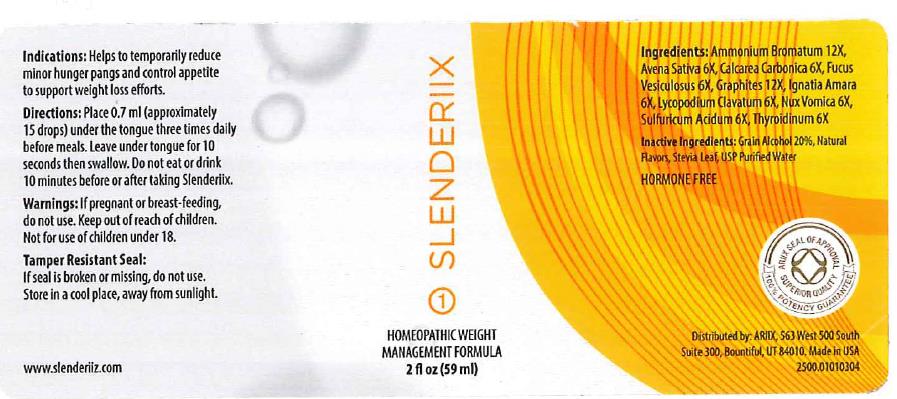 DRUG LABEL: Slenderiix
NDC: 64616-077 | Form: LIQUID
Manufacturer: Vitality Works
Category: homeopathic | Type: HUMAN OTC DRUG LABEL
Date: 20251217

ACTIVE INGREDIENTS: SULFURIC ACID 6 [hp_X]/1 mL; OYSTER SHELL CALCIUM CARBONATE, CRUDE 6 [hp_X]/1 mL; LYCOPODIUM CLAVATUM SPORE 6 [hp_X]/1 mL; AMMONIUM BROMIDE 12 [hp_X]/1 mL; STRYCHNOS NUX-VOMICA SEED 6 [hp_X]/1 mL; AVENA SATIVA FLOWERING TOP 6 [hp_X]/1 mL; GRAPHITE 12 [hp_X]/1 mL; THYROID, UNSPECIFIED 6 [hp_X]/1 mL; STRYCHNOS IGNATII SEED 6 [hp_X]/1 mL; FUCUS VESICULOSUS 6 [hp_X]/1 mL
INACTIVE INGREDIENTS: GLYCERIN; WATER; ALCOHOL; PEPPERMINT OIL; STEVIA LEAF; PROPYLENE GLYCOL

Slenderiix

ACTIVE INGREDIENT

Ammonium Bromatum 12X

Avena Sativa 6X

Calcarea Carbomica 6x

Focus Vesiculous 6X

Graphites 12 X

Ignata Amara 6X

Lycopodium Clavatum 6X

Nux Vomica 6X

Sulfuricum Acidum 6X

Thyroiinum 6X

INACTIVE INGREDIENT

Grain Alcohol (20% by volume), Natural Flavors, Stevia Leaf, USP Purified Water

WARNINGS

If pregnant or breast-feeding, do not use. Not for use by children under 18.

Keep out of reach of children.

INDICATIONS AND USAGE

Helps to temporarily reduce minor hunger pangs and control appetite to support weight loss efforts

DOSAGE AND ADMINISTRATION

Adults place 10-15 drops under the tongue three times per day. Leave uner tongue for 10 seconds, then swallow. Do Not eat or drink 10 minutes before or after taking the drops.

PURPOSE

Weight Management formula